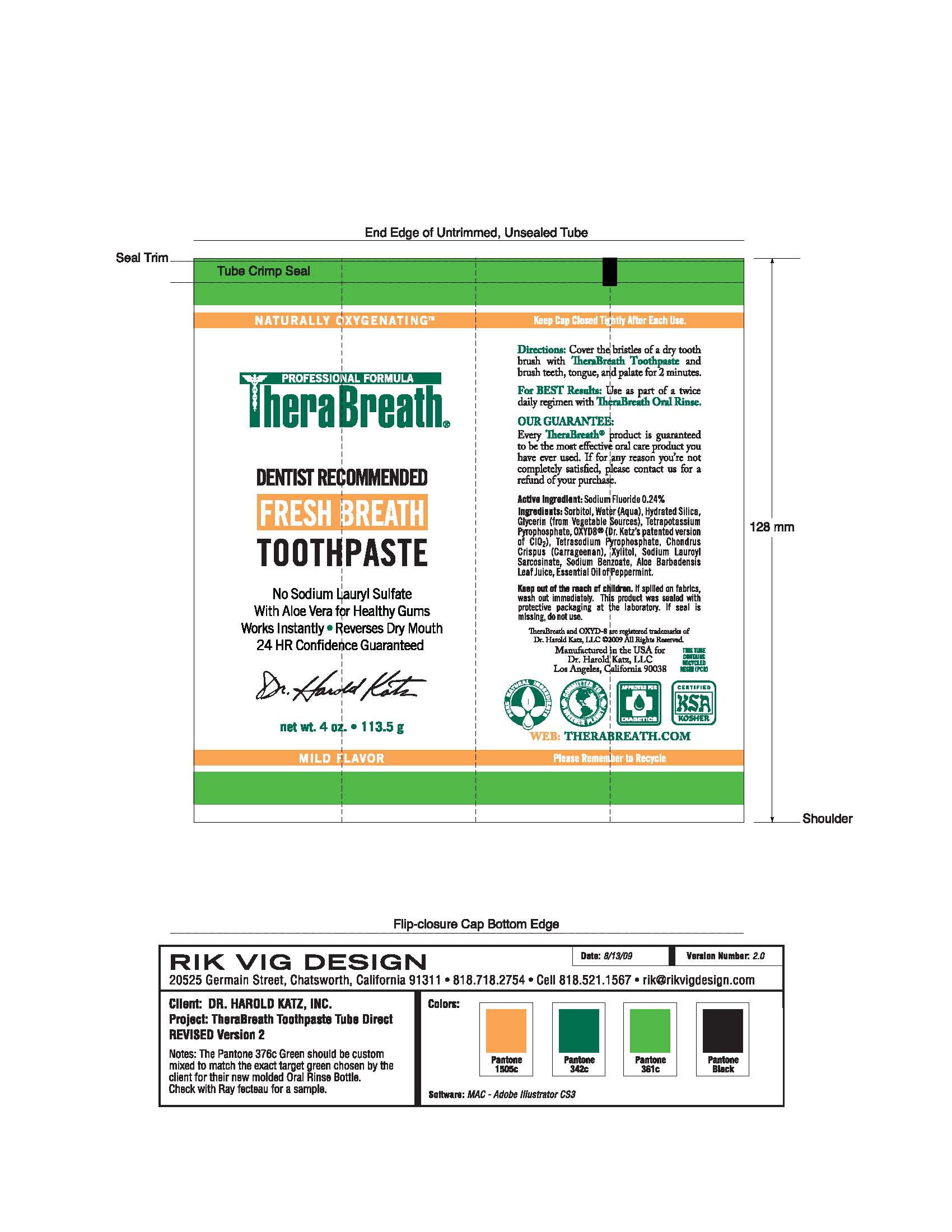 DRUG LABEL: THERABREATH TOOTHPASTE
NDC: 57367-033 | Form: GEL, DENTIFRICE
Manufacturer: 220 LABORATORIES INC
Category: otc | Type: HUMAN OTC DRUG LABEL
Date: 20100303

ACTIVE INGREDIENTS: SODIUM FLUORIDE 24 mg/10 g
INACTIVE INGREDIENTS: WATER; SORBITOL; SILICON DIOXIDE; GLYCERIN; SODIUM PYROPHOSPHATE; CARRAGEENAN; XYLITOL; SODIUM LAUROYL SARCOSINATE; SODIUM BENZOATE; SODIUM CHLORITE; ALOE

ThereBreath Packaging

INDICATIONS AND USAGE

Directions: Cover the bristles of a dry tooth brush with TheraBreath Toothpaste and brush teeth, tongue, and palate for 2 minutes.

Keep out of reach of children.

GENERAL PRECAUTIONS

If spilled on fabrics, wash out immediately. This product was sealed with protective packaging at the laboratory. If seal is missing, do not use.

PACKAGE LABEL

Naturally Oxygenating
Professional Formula
TheraBreath
Dentist Recommended
Fresh Breath
Toothpaste
No Sodium Lauryl Sulfate
With Aloe Vera for Health Gums
Works Instantly - Reverses Dry Mouth
24 HR Confidence Guaranteed